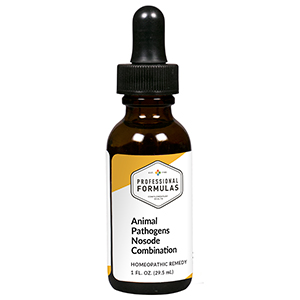 DRUG LABEL: Animal Pathogens Nosode Combination
NDC: 63083-9419 | Form: LIQUID
Manufacturer: Professional Complementary Health Formulas
Category: homeopathic | Type: HUMAN OTC DRUG LABEL
Date: 20190815

ACTIVE INGREDIENTS: BAPTISIA TINCTORIA WHOLE 3 [hp_X]/29.5 mL; GELSEMIUM SEMPERVIRENS ROOT 3 [hp_X]/29.5 mL; STRYCHNOS IGNATII SEED 6 [hp_X]/29.5 mL; PHOSPHORUS 6 [hp_X]/29.5 mL; PASTEURELLA MULTOCIDA 12 [hp_X]/29.5 mL; FRANCISELLA TULARENSIS 12 [hp_X]/29.5 mL
INACTIVE INGREDIENTS: ALCOHOL; WATER

R419

ACTIVE INGREDIENTS

Baptisia tinctoria 3X
Gelsemium sempervirens 3X
Ignatia amara 6X
Phosphorus 6X
Pasteurellose 12X
Tularemia 12X

QUESTIONS

Professional Formulas

PO Box 2034 Lake Oswego, OR 97035

INDICATIONS

For the temporary relief of occasional headache, minor muscle or joint pain, fatigue, or skin irritations.*

PURPOSE

*Claims based on traditional homeopathic practice, not accepted medical evidence. Not FDA evaluated.

WARNINGS

Persistent symptoms may be a sign of a serious condition. If symptoms persist or are accompanied by a fever, rash, or persistent headache, consult a doctor. Keep out of the reach of children. In case of overdose, get medical help or contact a poison control center right away. If pregnant or breastfeeding, ask a healthcare professional before use.

Keep out of the reach of children.

PREGNANCY OR BREAST FEEDING

If pregnant or breastfeeding, ask a healthcare professional before use.

DIRECTIONS

Place drops under tongue 30 minutes before/after meals. Adults and children 12 years and over: Take 10 to 15 drops once weekly or monthly. If mild symptoms are present, take 10 drops up to 3 times per day. Consult a physician for use in children under 12 years of age.

OTHER INFORMATION

Tamper resistant. If seal is broken, do not use. After opening, close container tightly and store at room temperature away from heat.

INACTIVE INGREDIENTS

40% ethanol, purified water.

LABEL

Est 1985

Professional Formulas

Complementary Health

Animal Pathogens Nosode Combination

Homeopathic Remedy

1 FL. OZ. (29.5 mL)